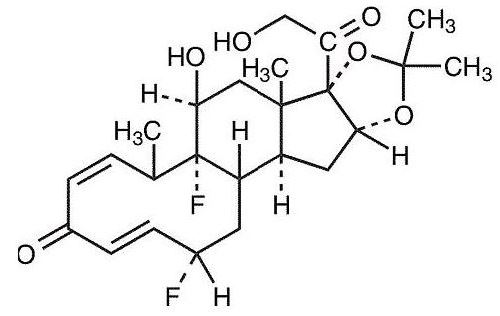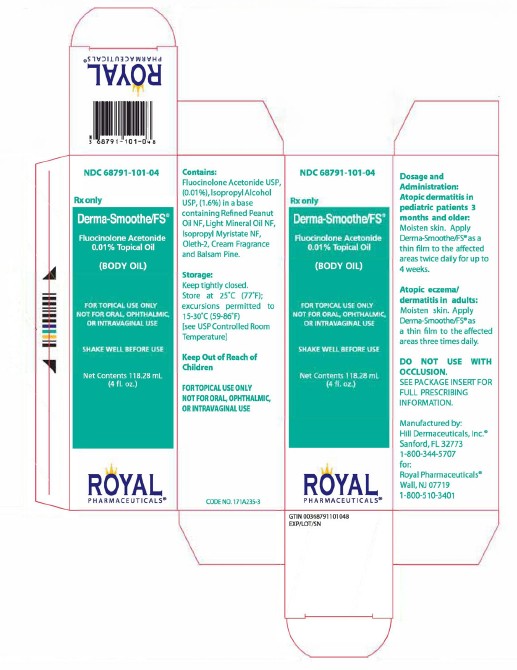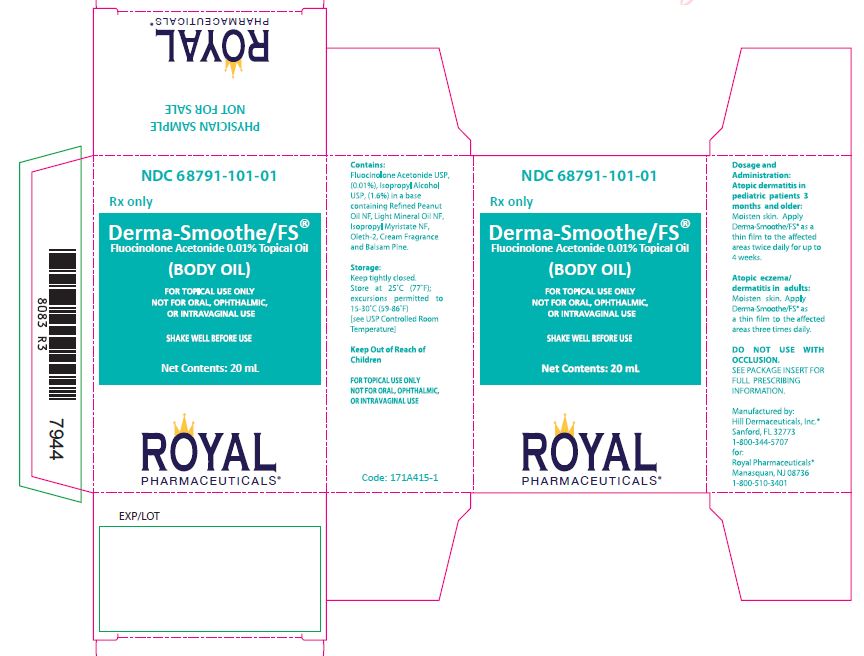 DRUG LABEL: Derma-Smoothe/FS
NDC: 68791-101 | Form: OIL
Manufacturer: Royal Pharmaceuticals
Category: prescription | Type: HUMAN PRESCRIPTION DRUG LABEL
Date: 20250630

ACTIVE INGREDIENTS: fluocinolone acetonide 0.11 mg/1 mL
INACTIVE INGREDIENTS: ISOPROPYL ALCOHOL; ISOPROPYL MYRISTATE; LIGHT MINERAL OIL; OLETH-2; PEANUT OIL

HIGHLIGHTS OF PRESCRIBING INFORMATION

These highlights do not include all the information needed to use Derma-Smoothe/FS® safely and effectively. See full prescribing information for Derma-Smoothe/FS®.
Derma-Smoothe/FS® (fluocinolone acetonide) Topical Oil, 0.01%
(Body Oil)
For Topical Use Only
Not for Oral, Ophthalmic, or Intravaginal Use
NDC 68791-101-04
Initial U.S. Approval: 1988

RECENT MAJOR CHANGES

Indication and Usage, Pediatric Patients with Atopic Dermatitis (1.2) 11/2007

1 INDICATIONS AND USAGE

Derma-Smoothe/FS® is a corticosteroid indicated for the

- topical treatment of atopic dermatitis in adult patients (1.1)
- topical treatment of moderate to severe atopic dermatitis in pediatric patients 3 months and older for up to 4 weeks (1.2)

Limitations of Use:

- Apply the least amount to cover affected areas.
  Discontinue when disease is controlled. (1.3)
- Do not use in the diaper area. (1.3)
- Do not use on the face, axillae, or groin. (1.3, 6.2, 8.4)

2 DOSAGE AND ADMINISTRATION

Derma-Smoothe/FS® is not for oral, ophthalmic, or intravaginal use.(2)

- Adult patients: Apply to affected areas 3 times daily. (2.1)
- Pediatric patients: Moisten skin and apply to affected areas twice daily for up to 4 weeks. (2.2)

3 DOSAGE FORMS AND STRENGTHS

Derma-Smoothe/FS® (fluocinolone acetonide) Topical Oil, 0.01% (Body Oil) is supplied in bottles containing 4 fluid ounces. (3)

4 CONTRAINDICATIONS

None (4)

5 WARNINGS AND PRECAUTIONS

- Topical corticosteroids can produce reversible HPA axis suppression, Cushing's syndrome, hyperglycemia, and glucosuria. (5.1)
- Systemic absorption may require evaluation for hypothalamic-pituitary-adrenal (HPA) axis suppression. (5.1)
- Modify use should HPA axis suppression develop. (5.1)
- Potent corticosteroids use on large areas, prolonged use or occlusive use may increase systemic absorption. (5.1)
- Local adverse reactions may include atrophy, striae, irritation, acneiform eruptions, hypopigmentation, and allergic contact dermatitis and may be more likely with occlusive use or more potent corticosteroids (5.2,5.3,6.1)
- Children may be more susceptible to systemic toxicity from equivalent doses. (5.1,8.4)

6 ADVERSE REACTIONS

The most common adverse reactions (≥ 5%) were cough (20%), rhinorrhea (13%), pyrexia (10%), telangiectasia (7%), nasopharyngitis (7%), and hypopigmentation (7%).

To report SUSPECTED ADVERSE REACTIONS, contact Hill Dermaceuticals, Inc. at 1-800-344-5707 or FDA at 1-800-FDA-1088 or www.fda.gov/medwatch.

FULL PRESCRIBING INFORMATION

1 INDICATIONS AND USAGE

1.1 Adult Patients with Atopic Dermatitis

Derma-Smoothe/FS® is indicated for the topical treatment of atopic dermatitis in adult patients.

1.2 Pediatric Patients with Atopic Dermatitis

Derma-Smoothe/FS® is indicated for the topical treatment of moderate to severe atopic dermatitis in pediatric patients, 3 months and older for up to 4 weeks. Safety and effectiveness in pediatric patients younger than 3 months of age have not been established.

1.3 Limitations of Use

Apply the least amount of Derma-Smoothe/FS® needed to cover the affected areas. As with other corticosteroids, Derma-Smoothe/FS® should be discontinued when control of disease is achieved. Contact the physician if no improvement is seen within 2 weeks.

Derma-Smoothe/FS® should not be applied to the diaper area; diapers or plastic pants may constitute occlusive use.

Derma-Smoothe/FS® should not be used on the face, axillae, or groin unless directed by the physician. Application to intertriginous areas should be avoided due to the increased risk of local adverse reactions. [see Adverse Reactions (6) and Use in Specific Populations (8.4)].

2 DOSAGE AND ADMINISTRATION

Derma-Smoothe/FS® is not for oral, ophthalmic, or intravaginal use.

The dosing of Derma-Smoothe/FS® is different for adult and pediatric patients.

2.1 Adult Patients with Atopic Dermatitis

Apply Derma-Smoothe/FS® as a thin film to the affected areas three times daily.

2.2 Pediatric Patients with Atopic Dermatitis

Moisten skin and apply Derma-Smoothe/FS® as a thin film to the affected areas twice daily for up to four weeks.

3 DOSAGE FORMS AND STRENGTHS

Derma-Smoothe/FS® (fluocinolone acetonide), Topical Oil, 0.01% (Body Oil) is supplied in bottles containing 4 fluid ounces.

4 CONTRAINDICATIONS

None.

5 WARNINGS AND PRECAUTIONS

5.1 Hypothalamic-Pituitary-Adrenal Axis Suppression

Systemic absorption of topical corticosteroids can produce reversible hypothalamic-pituitary-adrenal (HPA) axis suppression with the potential for glucocorticosteroid insufficiency. Cushing's syndrome, hyperglycemia, and glucosuria can also be produced by systemic absorption of topical corticosteroids.

Because of the potential for systemic absorption, use of topical corticosteroids may require that patients be periodically evaluated for HPA axis suppression. The ACTH stimulation test may be helpful in evaluating patients for HPA axis suppression.

If HPA axis suppression is documented, an attempt should be made to withdraw the drug, to reduce the frequency of application, or to substitute a less potent corticosteroid. Recovery of HPA axis function is generally prompt upon discontinuation of topical corticosteroids.

Conditions which increase systemic absorption include the use of more potent corticosteroids, use over large surface areas, use over prolonged periods, and use of occlusive dressings. Manifestations of adrenal insufficiency may require supplemental systemic corticosteroids.

Children may be more susceptible to systemic toxicity from equivalent doses due to their larger skin surface to body mass ratios. [See Use in Specific Populations (8.4)]

5.2 Local Adverse Reactions with Topical Corticosteroids

Local adverse reactions may occur with use of topical corticosteroids and may be more likely to occur with occlusive use, prolonged use or use of higher potency corticosteroids. Some local adverse reactions may be irreversible. Reactions may include atrophy, striae, telangiectasias, burning, itching, irritation, dryness, folliculitis, acneiform eruptions, hypopigmentation, perioral dermatitis, allergic contact dermatitis, secondary infection, and miliaria. [See Adverse Reactions (6.1)]

5.3 Allergic Contact Dermatitis with Topical Corticosteroids

Allergic contact dermatitis to any component of topical corticosteroids is usually diagnosed by a failure to heal rather than a clinical exacerbation. Clinical diagnosis of allergic contact dermatitis can be confirmed by patch testing.

5.4 Concomitant Skin Infections

Concomitant skin infections should be treated with an appropriate antimicrobial agent. If the infection persists unchanged, Derma-Smoothe/FS® should be discontinued until the infection has been adequately treated.

5.5 Use in Peanut-Sensitive Individuals

Physicians should use caution in prescribing Derma-Smoothe/FS® for peanut-sensitive individuals. [See Description (11)]

Should signs of hypersensitivity present (wheal and flare reactions, pruritus, or other manifestations), or should disease exacerbations occur, Derma-Smoothe/FS® should be discontinued immediately and appropriate therapy instituted.

6 ADVERSE REACTIONS

Because clinical trials are conducted under widely varying conditions, adverse reaction rates observed in the clinical trials of a drug cannot be directly compared to rates in the clinical trials of another drug and may not reflect the rates observed in practice.

6.1 Clinical Studies Experience: Evaluation of Facial Use in Pediatric Subjects

An open-label study was conducted in 58 children with moderate to severe atopic dermatitis (2 to 12 years old) to evaluate the safety of Derma-Smoothe/FS® when applied to the face twice daily for 4 weeks. The following adverse reactions were reported:

Incidence of Adverse Reactions (%), N=58
Adverse Reaction (AR) [The number of individual adverse reactions reported does not necessarily reflect the number of individual subjects, since one subject could have multiple reporting of an adverse reaction.] | # of subjects (%) | Day 14 | Day 28 [End of Treatment] | Day 56 [Four Weeks Post Treatment]
Any AE | 15 (26) | 6 (10) | 7 (12) | 7 (12)
Telangiectasia | 5 (9) | 3 (5) | 4 (7) | 2 (4)
Erythema | 3 (5) |  |  | 3 (5)
Itching | 3 (5) |  |  | 3 (5)
Irritation | 3 (5) |  |  | 3 (5)
Burning | 3 (5) |  |  | 3 (5)
Hypopigmentation | 2 (4) | 2 (4)
Shiny skin | 1 (2) |  | 1 (2)
Secondary atopic dermatitis | 1 (2) |  |  | 1 (2)
Papules and pustules | 1 (2) |  |  | 1 (2)
Keratosis pilaris | 1 (2) |  |  | 1 (2)
Folliculitis | 1 (2) |  | 1 (2)
Facial herpes simplex | 1 (2) | 1 (2)
Acneiform eruption | 1 (2) |  | 1 (2)
Ear infection | 1 (2) |  | 1 (2)

6.2 Clinical Studies Experience: Evaluation in Pediatric Subjects 3 months to 2 years old

An open-label safety study was conducted in 29 children to assess the HPA axis by ACTH stimulation testing following use of Derma-Smoothe/FS® twice daily for 4 weeks. The following adverse reactions were reported in the study [See Use in Specific Populations (8.4)];

Adverse Reactions (%), N=30 [Includes one subject who withdrew at Week 2]
Adverse Reaction | # of subjects (%)
Diarrhea | 1 (3)
Vomiting | 1 (3)
Pyrexia | 3 (10)
Abscess | 1 (3)
Molluscum | 1 (3)
Nasopharyngitis | 2 (7)
URI | 1 (3)
Otitis media | 1 (3)
Cough | 6 (20)
Rhinorrhea | 4 (13)
Atopic dermatitis | 1 (3)
Eczema | 1 (3)
Hyperpigmentation | 1 (3)
Hypopigmentation | 2 (7)
Rash | 1 (3)

8 USE IN SPECIFIC POPULATIONS

8.1 Pregnancy

TERATOGENIC EFFECTS

Pregnancy Category C: Corticosteroids have been shown to be teratogenic in laboratory animals when administered systemically at relatively low dosage levels. Some corticosteroids have been shown to be teratogenic after dermal application in laboratory animals.

There are no adequate and well-controlled studies in pregnant women on teratogenic effects from Derma-Smoothe/FS®. Therefore, Derma-Smoothe/FS® should be used during pregnancy only if the potential benefit justifies the potential risk to the fetus.

8.3 Nursing Mothers

Systemically administered corticosteroids appear in human milk and could suppress growth, interfere with endogenous corticosteroid production, or cause other untoward effects. It is not known whether topical administration of corticosteroids could result in sufficient systemic absorption to produce detectable quantities in human milk.

Because many drugs are excreted in human milk, caution should be exercised when Derma-Smoothe/FS® is administered to a nursing woman.

8.4 Pediatric Use

8.4.1 Systemic Adverse Reactions in Pediatric Patients

HPA axis suppression, Cushing's syndrome, and intracranial hypertension have been reported in children receiving topical corticosteroids. Manifestations of adrenal suppression in children include linear growth retardation, delayed weight gain, low plasma cortisol levels, and subnormal response to ACTH stimulation. Manifestations of intracranial hypertension include bulging fontanelles, headaches, and bilateral papilledema.

Because of a higher ratio of skin surface area to body mass, children are at a greater risk for systemic adverse reactions than are adults when treated with topical corticosteroids. [See Warnings and Precautions (5.1)]

8.4.2 Evaluation in Peanut-Sensitive Pediatric Subjects

A clinical study was conducted to assess the safety of Derma-Smoothe/FS®, which contains refined peanut oil, on subjects with known peanut allergies. The study enrolled 13 subjects with atopic dermatitis, 6 to 17 years of age. Of the 13 subjects, 9 were Radioallergosorbent Test (RAST) positive to peanuts and 4 had no peanut sensitivity (controls). The study evaluated the subjects' responses to both prick test and patch test utilizing peanut oil NF, Derma-Smoothe/FS® and histamine/saline controls. Subjects were also treated with Derma-Smoothe/FS® twice daily for 7 days. Prick test and patch test results for all 13 patients were negative to Derma-Smoothe/FS® and the refined peanut oil. One of the 9 peanut-sensitive patients experienced an exacerbation of atopic dermatitis after 5 days of Derma-Smoothe/FS®. The bulk peanut oil NF, used in Derma-Smoothe/FS® is heated at 475°F for at least 15 minutes, which should provide for adequate decomposition of allergenic proteins. [See Description (11)]

8.4.3 Evaluation in Pediatric Subjects 2 to 6 years old

Open-label safety studies were conducted on 33 children (20 subjects ages 2 to 6 years, 13 subjects ages 7 to 12 years) with moderate to severe stable atopic dermatitis. Subjects were treated with Derma-Smoothe/FS® twice daily for 4 weeks. Baseline body surface area involvement was 50% to 75% in 15 subjects and greater than 75% in 18 subjects. Morning pre-stimulation cortisol and post-ACTH stimulation cortisol levels were obtained in each subject at the beginning of the trial and at the end of 4 weeks of treatment. At the end of treatment, 4 out of 18 subjects aged 2 to 5 years showed low pre-stimulation cortisol levels (3.2 to 6.6 µg/dL; normal: cortisol > 7µg/dL) but all had normal responses to 0.25 mg of ACTH stimulation (cortisol > 18 µg/dL).

8.4.4 Evaluation in Pediatric Subjects 3 months to 2 years old

An open-label safety study was conducted in 29 children (7 subjects ages 3 to 6 months, 7 subjects ages > 6 to 12 months and 15 subjects ages > 12 months to 2 years of age) to assess the HPA axis by ACTH stimulation testing following use of Derma-Smoothe/FS® twice daily for 4 weeks. All subjects had moderate to severe atopic dermatitis with disease involvement on at least 20% body surface area. Baseline body surface area involvement was 50% to 75% in 11 subjects and greater than 75% in 7 subjects. Morning pre-stimulation and post-ACTH stimulation cortisol levels were obtained in each subject at the beginning of the trial and at the end of 4 weeks of treatment. All subjects had normal responses to 0.125 mg of ACTH stimulation (cortisol > 18 µg/dL).

10 OVERDOSAGE

Topically applied corticosteroids can be absorbed in sufficient amounts to produce systemic effects, including under conditions of normal use. [See Warnings and Precautions (5.1) and Use in Specific Populations (8.4)].

11 DESCRIPTION

Derma-Smoothe/FS® (fluocinolone acetonide), Topical Oil, 0.01% (Body Oil) contains fluocinolone acetonide [(6α, 11β, 16α)-6,9-difluoro-11,21-dihydroxy-16,17 [(1-methylethylidene)bis(oxy)]-pregna-1,4-diene-3,20-dione, cyclic 16,17 acetal with acetone], a synthetic corticosteroid for topical dermatologic use.

This formulation is also marketed as Derma-Smoothe/FS® (fluocinolone acetonide), Topical Oil, 0.01% (Scalp Oil) for use with shower caps for treatment of scalp psoriasis in adults, and as fluocinolone acetonide oil, 0.01% for treatment of chronic eczematous external otitis. Chemically, fluocinolone acetonide is C24 H30 F2 O6. It has the following structural formula:

Fluocinolone acetonide in Derma-Smoothe/FS® has a molecular weight of 452.50. It is a white crystalline powder that is odorless, stable in light, and melts at 270°C with decomposition; soluble in alcohol, acetone and methanol; slightly soluble in chloroform; insoluble in water.

Each gram of Derma-Smoothe/FS® contains approximately 0.11 mg of fluocinolone acetonide in a blend of oils, which contains isopropyl alcohol, isopropyl myristate, light mineral oil, oleth-2, refined peanut oil NF and fragrances.

Derma-Smoothe/FS® is formulated with 48% refined peanut oil NF. The peanut oil used in Derma-Smoothe/FS® is tested for peanut proteins through amino acid analysis which can detect the quantity of amino acids to below 0.5 parts per million.

12 CLINICAL PHARMACOLOGY

12.1 Mechanism of Action

Like other topical corticosteroids, fluocinolone acetonide has anti-inflammatory, antipruritic, and vasoconstrictive properties. The mechanism of the anti-inflammatory activity of the topical steroids, in general, is unclear. However, corticosteroids are thought to act by the induction of phospholipase A2 inhibitory proteins, collectively called lipocortins. It is postulated that these proteins control the biosynthesis of potent mediators of inflammation such as prostaglandins and leukotrienes by inhibiting the release of their common precursor arachidonic acid. Arachidonic acid is released from membrane phospholipids by phospholipase A2.

12.3 Pharmacokinetics

Topical corticosteroids can be absorbed from intact healthy skin. The extent of percutaneous absorption of topical corticosteroids is determined by many factors, including the product formulation and the integrity of the epidermal barrier. Occlusion, inflammation and/or other disease processes in the skin may increase percutaneous absorption.

The use of pharmacodynamic endpoints for assessing the systemic exposure of topical corticosteroids may be necessary due to the fact that circulating levels are often below the level of detection. Once absorbed through the skin, topical corticosteroids are metabolized primarily in the liver, and are then excreted by the kidneys. Some corticosteroids and their metabolites are also excreted in the bile.

Derma-Smoothe/FS® is in the low to medium range of potency as compared with other topical corticosteroids in vasoconstrictor studies.

13 NONCLINICAL TOXICOLOGY

13.1 Carcinogenesis, mutagenesis, impairment of fertility

Long-term animal studies have not been performed to evaluate the carcinogenic potential or the effect on fertility of Derma-Smoothe/FS®. Studies have not been performed to evaluate the mutagenic potential of fluocinolone acetonide, the active ingredient in Derma-Smoothe/FS®. Some corticosteroids have been found to be genotoxic in various genotoxicity tests (i.e. the in vitro human peripheral blood lymphocyte chromosome aberration assay with metabolic activation, the in vivo mouse bone marrow micro nucleus assay, the Chinese hamster micronucleus test, and the in vitro mouse lymphoma gene mutation assay).

16 HOW SUPPLIED / STORAGE AND HANDLING

Derma-Smoothe/FS® is supplied in bottles containing 4 fluid ounces. It is labeled as Body Oil (NDC # 68791-101-04).

STORAGE AND HANDLING

Storage: Store at 25°C (68°-77°F); excursions permitted to 15°-30°C (59°-86°F) [See USP Controlled Room Temperature].

17 PATIENT COUNSELING INFORMATION

17.1 Instructions

- Derma-Smoothe/FS® should be used as directed by the physician. It is for external use only. Avoid contact with the eyes. In case of contact, wash eyes liberally with water.
- Derma-Smoothe/FS® should not be used for any disorder other than that for which it was prescribed.
- Patients should report any worsening of their skin condition to their physician promptly.
- Derma-Smoothe/FS® should not be applied under occlusion unless directed by the physician. Derma-Smoothe/FS® should not be applied to the diaper area as diapers or plastic pants may constitute occlusive use.
- Derma-Smoothe/FS® should not be used on the face, axillae, or groin unless directed by the physician.
- As with other corticosteroids, therapy should be discontinued when control of disease is achieved. Contact the physician if no improvement is seen within 2 weeks.
- Do not use other corticosteroid-containing products while using Derma-Smoothe/FS® without first consulting your physician.

Manufactured by:
Hill Dermaceuticals, Inc.®
Sanford, FL 32773
1.800.344.5707

For: Royal Pharmaceuticals, Inc
Wall, NJ 07719
1.800.510.3401

Rev. CODE 171A240-2
Date: 08/2024

PRINCIPAL DISPLAY PANEL - 118.28 mL Carton Label

NDC 68791-101-04

Rx only

Derma-Smoothe/FS®

Fluocinolone Acetonide

0.01% Topical Oil

(Body Oil)

FOR TOPICAL USE ONLY

NOT FOR ORAL, OPHTHALMIC,

or INTRAVAGINAL USE

SHAKE WELL BEFORE USE

Net Contents 118.28 mL

(4 fl. oz.)

ROYAL

PHARMACEUTICALS®

PRINCIPAL DISPLAY PANEL - 20 mL Carton Physcian Sample Label

NOT FOR SALE

PHYSICIAN SAMPLE

NDC 68791-101-01

Rx only

Derma-Smoothe/FS®

Fluocinolone Acetonide 0.01% Topical Oil

(BODY OIL)

FOR TOPICAL USE ONLY

NOT FOR ORAL OPHTHALMIC,

OR INTRAVAGINAL USE

SHAKE WELL BEFORE USE

NET Contents: 20 mL

Royal Pharmaceuticals®